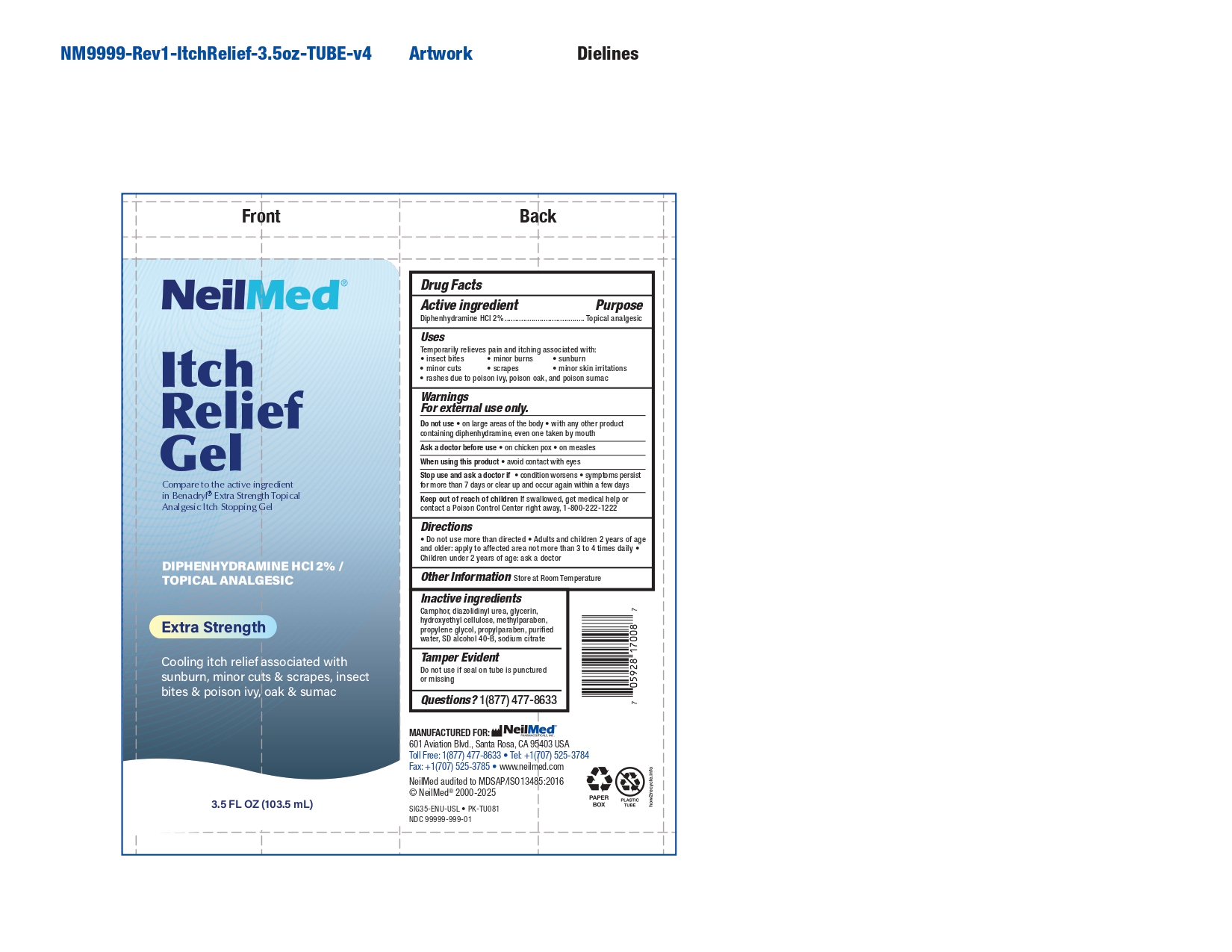 DRUG LABEL: Itch Relief
NDC: 13709-351 | Form: GEL
Manufacturer: Neilmed Pharmaceuticals Inc.
Category: otc | Type: HUMAN OTC DRUG LABEL
Date: 20251126

ACTIVE INGREDIENTS: DIPHENHYDRAMINE HYDROCHLORIDE 20 mg/1 mL
INACTIVE INGREDIENTS: SODIUM CITRATE, UNSPECIFIED FORM; DIAZOLIDINYL UREA; METHYLPARABEN; GLYCERIN; PROPYLENE GLYCOL; CAMPHOR (SYNTHETIC); HYDROXYETHYL CELLULOSE (140 CPS AT 5%); WATER; PROPYLPARABEN; ALCOHOL

Itch Relief

Drug Facts: Active Ingredients

Diphenhydramine HCl 2%

Purpose

Topical analgesic

Uses

Temporarily relieves pain and itching associated with:

- insect bites
- minor burns
- sunburn
- minor cuts
- scrapes
- minor skin irritations
- rashes due to poison ivy, poison oak and poison sumac

Warnings

For external use only

Do not use

- on large areas of the body
- with any other product containing diphenhydramine, even one taken by mouth

When using this product

- avoid contact with eyes

Stop use and ask a doctor if

- condition worsens
- symptoms persist for more than 7 days or clear up and occur again within a few days

Keep out of reach of children If

swallowed, get medical help or contact a Poison Control Center right away, 1-800-222-1222

Directions

- Do not use more than directed
- Adults and children 2 years of age and older: apply to affected area not more than 3 to 4 times daily
- Children under 2 years of age: ask a doctor

Other Information

Store at Room Temperature

Inactive ingredients

- Camphor
- diazolidinyl urea
- glycerin
- hydroxyethyl cellulose
- methylparaben
- propylene glycol
- propylparaben
- purified water
- SD alcohol 40-B
- sodium citrate

Tamper Evident

Do not use if seal on tube is punctured or missing

Questions?

1(877) 477-8633